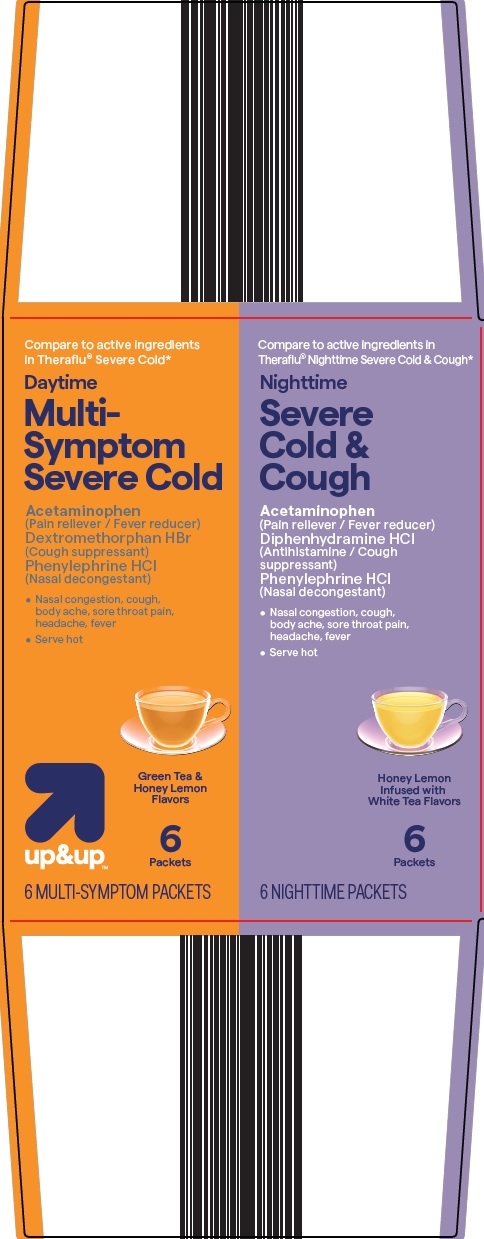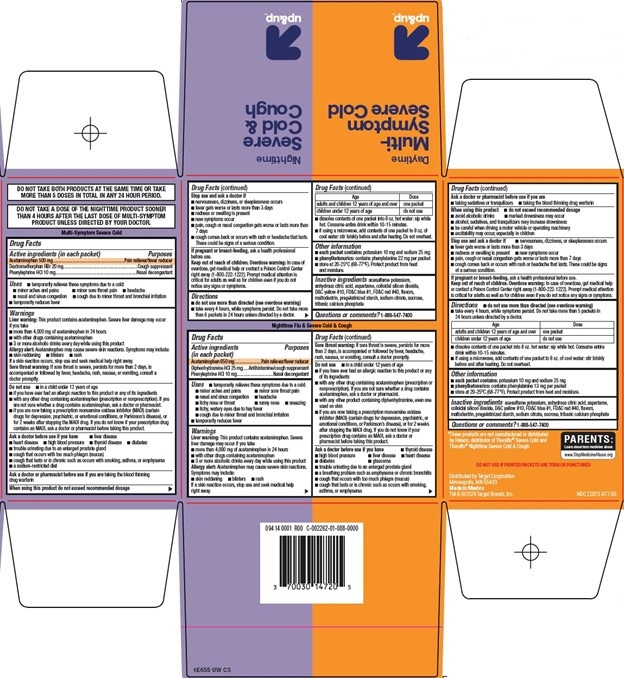 DRUG LABEL: Up and Up Daytime Multi Symptom Severe Cold Nighttime Severe Cold and Cough
NDC: 11673-877 | Form: KIT | Route: ORAL
Manufacturer: Target Corporation
Category: otc | Type: HUMAN OTC DRUG LABEL
Date: 20251124

ACTIVE INGREDIENTS: ACETAMINOPHEN 500 mg/1 1; DEXTROMETHORPHAN HYDROBROMIDE 20 mg/1 1; PHENYLEPHRINE HYDROCHLORIDE 10 mg/1 1; ACETAMINOPHEN 650 mg/1 1; DIPHENHYDRAMINE HYDROCHLORIDE 25 mg/1 1; PHENYLEPHRINE HYDROCHLORIDE 10 mg/1 1
INACTIVE INGREDIENTS: ACESULFAME POTASSIUM; ANHYDROUS CITRIC ACID; ASPARTAME; SILICON DIOXIDE; D&C YELLOW NO. 10; FD&C BLUE NO. 1; FD&C RED NO. 40; MALTODEXTRIN; SODIUM CITRATE, UNSPECIFIED FORM; SUCROSE; TRIBASIC CALCIUM PHOSPHATE; ACESULFAME POTASSIUM; ANHYDROUS CITRIC ACID; ASPARTAME; SILICON DIOXIDE; D&C YELLOW NO. 10; FD&C BLUE NO. 1; FD&C RED NO. 40; MALTODEXTRIN; SODIUM CITRATE, UNSPECIFIED FORM; SUCROSE; TRIBASIC CALCIUM PHOSPHATE

Target Corporation Daytime Multi-Symptom Severe Cold/Nighttime Severe Cold and Cough Drug Facts

Active ingredients (in each packet) - Daytime

Acetaminophen 500 mg

Dextromethorphan HBr 20 mg

Phenylephrine HCl 10 mg

Purposes

Pain reliever/fever reducer

Cough suppressant

Nasal decongestant

Uses

- temporarily relieves these symptoms due to a cold:
- minor aches and pains
- minor sore throat pain
- headache
- nasal and sinus congestion
- cough due to minor throat and bronchial irritation
- temporarily reduces fever

Warnings

Liver warning: This product contains acetaminophen. Severe liver damage may occur if you take

- more than 4,000 mg of acetaminophen in 24 hours
- with other drugs containing acetaminophen
- 3 or more alcoholic drinks every day while using this product

Allergy alert: Acetaminophen may cause severe skin reactions. Symptoms may include:

- skin reddening
- blisters
- rash

If a skin reaction occurs, stop use and seek medical help right away.

Sore throat warning: If sore throat is severe, persists for more than 2 days, is accompanied or followed by fever, headache, rash, nausea, or vomiting, consult a doctor promptly.

Do not use

- in a child under 12 years of age
- if you have ever had an allergic reaction to this product or any of its ingredients
- with any other drug containing acetaminophen (prescription or nonprescription). If you are not sure whether a drug contains acetaminophen, ask a doctor or pharmacist.
- if you are now taking a prescription monoamine oxidase inhibitor (MAOI) (certain drugs for depression, psychiatric, or emotional conditions, or Parkinson’s disease), or for 2 weeks after stopping the MAOI drug. If you do not know if your prescription drug contains an MAOI, ask a doctor or pharmacist before taking this product.

Ask a doctor before use if you have

- liver disease
- heart disease
- high blood pressure
- thyroid disease
- diabetes
- trouble urinating due to an enlarged prostate gland
- cough that occurs with too much phlegm (mucus)
- cough that lasts or is chronic such as occurs with smoking, asthma, or emphysema
- a sodium-restricted diet

Ask a doctor or pharmacist before use if you are

taking the blood thinning drug warfarin

When using this product

do not exceed recommended dosage

Stop use and ask a doctor if

- nervousness, dizziness, or sleeplessness occurs
- fever gets worse or lasts more than 3 days
- redness or swelling is present
- new symptoms occur
- pain, cough or nasal congestion gets worse or lasts more than 7 days
- cough comes back or occurs with rash or headache that lasts. These could be signs of a serious condition.

If pregnant or breast-feeding,

ask a health professional before use.

Keep out of reach of children.

Overdose warning: In case of overdose, get medical help or contact a Poison Control Center right away (1-800-222-1222). Prompt medical attention is critical for adults as well as for children even if you do not notice any signs or symptoms.

Directions

- do not use more than directed (see overdose warning)
- take every 4 hours, while symptoms persist. Do not take more than 6 packets in 24 hours unless directed by a doctor.

Age | Dose
adults and children 12 years of age and over | one packet
children under 12 years of age | do not use

- dissolve contents of one packet into 8 oz. hot water: sip while hot. Consume entire drink within 10-15 minutes.
- if using a microwave, add contents of one packet to 8 oz. of cool water: stir briskly before and after heating. Do not overheat.

Other information

- each packet contains: potassium 10 mg and sodium 25 mg
- phenylketonurics: contains phenylalanine 22 mg per packet
- store at 20-25°C (68-77°F). Protect product from heat and moisture.

Inactive ingredients

acesulfame potassium, anhydrous citric acid, aspartame, colloidal silicon dioxide, D&C yellow #10, FD&C blue #1, FD&C red #40, flavors, maltodextrin, pregelatinized starch, sodium citrate, sucrose, tribasic calcium phosphate

Questions or comments?

1-888-547-7400

Active ingredients (in each packet) Nighttime

Acetaminophen 650 mg

Diphenhydramine HCl 25 mg

Phenylephrine HCl 10 mg

Purposes

Pain reliever/fever reducer

Antihistamine/cough suppressant

Nasal decongestant

Uses

- temporarily relieves these symptoms due to a cold:
- minor aches and pains
- minor sore throat pain
- nasal and sinus congestion
- headache
- itchy nose or throat
- runny nose
- sneezing
- itchy, watery eyes due to hay fever
- cough due to minor throat and bronchial irritation
- temporarily reduces fever

Warnings

Liver warning: This product contains acetaminophen. Severe liver damage may occur if you take

- more than 4,000 mg of acetaminophen in 24 hours
- with other drugs containing acetaminophen
- 3 or more alcoholic drinks every day while using this product

Allergy alert: Acetaminophen may cause severe skin reactions. Symptoms may include:

- skin reddening
- blisters
- rash

If a skin reaction occurs, stop use and seek medical help right away.

Sore throat warning: If sore throat is severe, persists for more than 2 days, is accompanied or followed by fever, headache, rash, nausea, or vomiting, consult a doctor promptly.

Do not use

- in a child under 12 years of age
- if you have ever had an allergic reaction to this product or any of its ingredients
- with any other drug containing acetaminophen (prescription or nonprescription). If you are not sure whether a drug contains acetaminophen, ask a doctor or pharmacist.
- with any other product containing diphenhydramine, even one used on skin
- if you are now taking a prescription monoamine oxidase inhibitor (MAOI) (certain drugs for depression, psychiatric, or emotional conditions, or Parkinson’s disease), or for 2 weeks after stopping the MAOI drug. If you do not know if your prescription drug contains an MAOI, ask a doctor or pharmacist before taking this product.

Ask a doctor before use if you have

- thyroid disease
- high blood pressure
- liver disease
- heart disease
- diabetes
- glaucoma
- trouble urinating due to an enlarged prostate gland
- a breathing problem such as emphysema or chronic bronchitis
- cough that occurs with too much phlegm (mucus)
- cough that lasts or is chronic such as occurs with smoking, asthma, or emphysema

Ask a doctor or pharmacist before use if you are

- taking sedatives or tranquilizers
- taking the blood thinning drug warfarin

When using this product

- do not exceed recommended dosage
- avoid alcoholic drinks
- marked drowsiness may occur
- alcohol, sedatives, and tranquilizers may increase drowsiness
- be careful when driving a motor vehicle or operating machinery
- excitability may occur, especially in children

Stop use and ask a doctor if

- nervousness, dizziness, or sleeplessness occurs
- fever gets worse or lasts more than 3 days
- redness or swelling is present
- new symptoms occur
- pain, cough or nasal congestion gets worse or lasts more than 7 days
- cough comes back or occurs with rash or headache that lasts. These could be signs of a serious condition.

If pregnant or breast-feeding,

ask a health professional before use.

Keep out of reach of children.

Overdose warning: In case of overdose, get medical help or contact a Poison Control Center right away (1-800-222-1222). Prompt medical attention is critical for adults as well as for children even if you do not notice any signs or symptoms.

Directions

- do not use more than directed (see overdose warning)
- take every 4 hours, while symptoms persist. Do not take more than 5 packets in 24 hours unless directed by a doctor.

Age | Dose
adults and children 12 years of age and over | one packet
children under 12 years of age | do not use

- dissolve contents of one packet into 8 oz. hot water: sip while hot. Consume entire drink within 10-15 minutes.
- if using a microwave, add contents of one packet to 8 oz. of cool water: stir briskly before and after heating. Do not overheat.

Other information

- each packet contains: potassium 10 mg and sodium 25 mg
- phenylketonurics: contains phenylalanine 13 mg per packet
- store at 20-25°C (68-77°F). Protect product from heat and moisture.

Inactive ingredients

acesulfame potassium, anhydrous citric acid, aspartame, colloidal silicon dioxide, D&C yellow #10, FD&C blue #1, FD&C red #40, flavors, maltodextrin, pregelatinized starch, sodium citrate, sucrose, tribasic calcium phosphate

Questions or comments?

1-888-547-7400

Package/Label Principal Display Panel

Compare to active ingredients in Theraflu® Severe Cold

Daytime Multi-Symptom Severe Cold

Acetaminophen (Pain reliever / Fever reducer)

Dextromethorphan HBr (Cough suppressant)

Phenylephrine HCl (Nasal decongestant)

• Nasal congestion, cough, body ache, sore throat pain, headache, fever

• Serve hot

Green Tea & Honey Lemon Flavors

up&up™

6 Packets

6 MULTI-SYMPTOM PACKETS

Compare to active ingredients in Theraflu® Nighttime Severe Cold & Cough

Nighttime Severe Cold & Cough

Acetaminophen (Pain reliever / Fever reducer)

Diphenhydramine HCl (Antihistamine / Cough suppressant)

Phenylephrine HCl (Nasal decongestant)

• Nasal congestion, cough, body ache, sore throat pain, headache, fever

• Serve hot

Honey Lemon Infused with White Tea Flavors

6 Packets

6 NIGHTTIME PACKETS